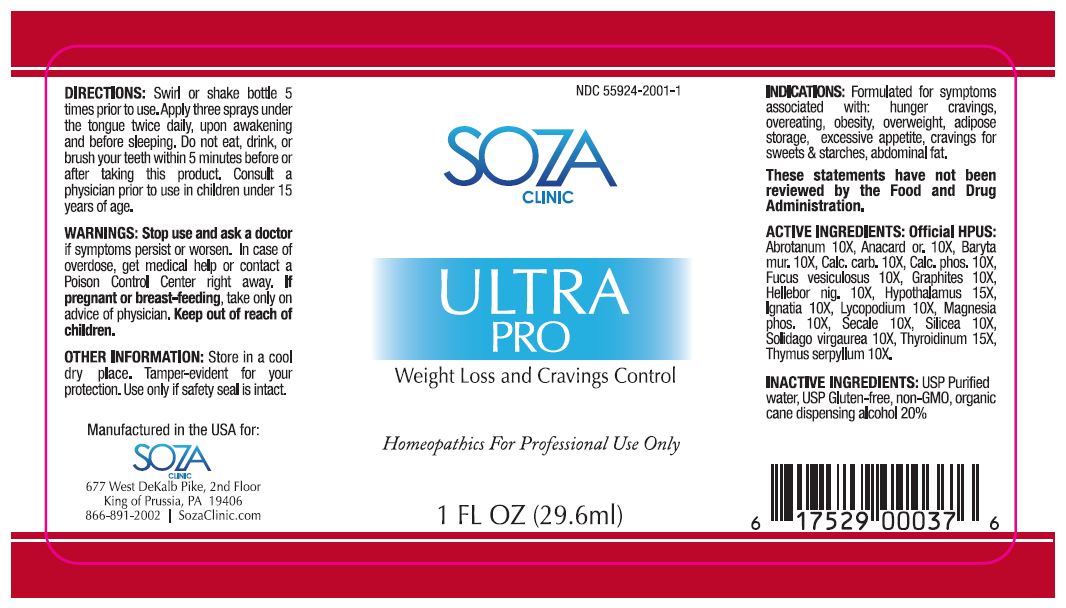 DRUG LABEL: ULTRA PRO 
NDC: 55924-2001 | Form: LIQUID
Manufacturer: SENA LLC
Category: homeopathic | Type: HUMAN OTC DRUG LABEL
Date: 20120724

ACTIVE INGREDIENTS: Artemisia Abrotanum Flowering Top 10 [hp_X]/1 mL; Semecarpus Anacardium Juice 10 [hp_X]/1 mL; Barium Chloride Dihydrate 10 [hp_C]/1 mL; Oyster Shell Calcium Carbonate, Crude 10 [hp_X]/1 mL; Tribasic Calcium Phosphate 10 [hp_X]/1 mL; Fucus Vesiculosus 10 [hp_X]/1 mL; Graphite 10 [hp_X]/1 mL; Helleborus Niger Root 10 [hp_X]/1 mL; Bos Taurus Hypothalamus 15 [hp_X]/1 mL; Strychnos Ignatii Seed 10 [hp_X]/1 mL; Lycopodium Clavatum Spore 10 [hp_X]/1 mL; Magnesium Phosphate, Dibasic Trihydrate 10 [hp_X]/1 mL; Claviceps Purpurea Sclerotium 10 [hp_X]/1 mL; Silicon Dioxide 10 [hp_X]/1 mL; Solidago Virgaurea Flowering Top 10 [hp_X]/1 mL; Thymus Serpyllum 10 [hp_X]/1 mL; Thyroid, Unspecified 15 [hp_X]/1 mL
INACTIVE INGREDIENTS: Water; Alcohol

Ultra Pro

Active Ingredients

Abrotanum 10X, Anacard or. 10X, Baryta mur. 10X, Calc. carb. 10X, Calc. phos. 10X, Fucus vesiculosus 10X, Graphites 10X, Hellebor nig. 10X, Hypothalamus 15X, Ignatia 10X, Lycopodium 10X, Magnesia phos. 10X, Secale 10X, Silicea 10X, Solidago virgaurea 10X, Thyroidinum 15X, Thymus serpyllum 10X

Indications

Formulated for symptoms associated with: hunger cravings, overeating, obesity, overweight, adipose storage, excessive appetite, cravings for sweets & starches, abdominal fat.

Warnings

Stop use and ask a doctor if symptoms persist or worsen.

Overdose

In case of overdose, get medical help or contact a Poison Control Center right away.

If pregnant or breast-feeding

Take only on advice of physician.

Keep out of reach of children.

Dosage and Administration

Swirl or shake bottle 5 times prior to use. Apply three sprays under the tongue twice daily, upon awakening and before sleeping. Do not eat, drink, or brush your teeth within 5 minutes before or after taking this product. Consult a physician prior to use in children under 15 years of age.

Inactive ingredients

USP Purified water, USP Gluten-free, non-GMO, organic cane dispensing alcohol 20%

Other Information

Store in a cool dry place.
Tamper-evident for your protection. Use only if safety seal is intact.

Questions

866-891-2002
SozaClinic.com

Principal Display Panel

NDC 55924-2001-1
SOZA CLINIC
ULTRA PRO
Weight Loss and Cravings Control
Homeopathics For Professional Use Only
1 FL OZ (29.6 ml)
Manufactured in the USA for:
SOZA CLINIC
677 West DeKalb Pike, 2nd Floor
King of Prussia, PA 19406
866-891-2002 | SozaClinic.com